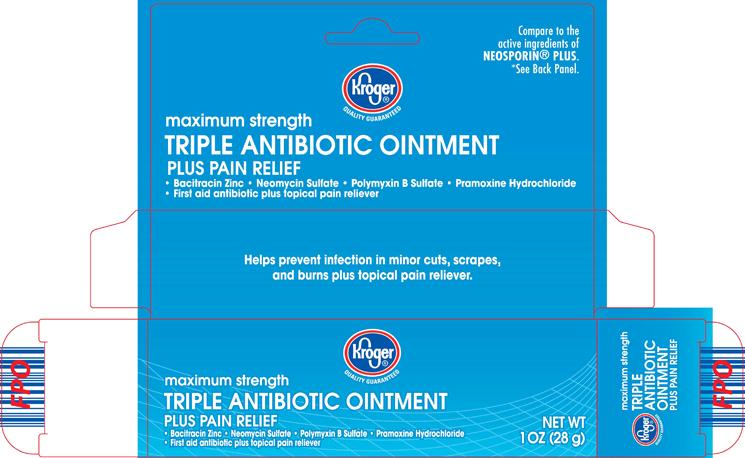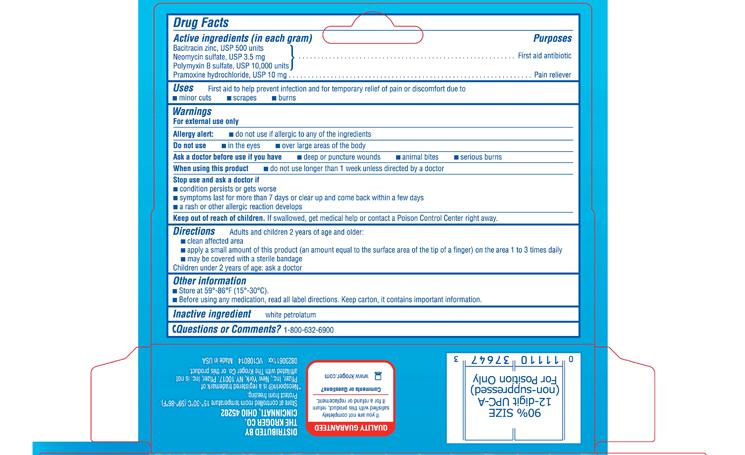 DRUG LABEL: Triple Antibiotic Plus
NDC: 59450-823 | Form: OINTMENT
Manufacturer: The Kroger Co.
Category: otc | Type: HUMAN OTC DRUG LABEL
Date: 20130320

ACTIVE INGREDIENTS: BACITRACIN ZINC 500 [USP'U]/1 g; NEOMYCIN SULFATE 3.5 mg/1 g; POLYMYXIN B SULFATE 10000 [USP'U]/1 g; PRAMOXINE HYDROCHLORIDE 10 mg/1 g
INACTIVE INGREDIENTS: PETROLATUM

Bacitracin Zinc, Neomycin Sulfate, Polymyxin B Sulfate, Pramoxine Hydrochloride

OTC - ACTIVE INGREDIENT

(in each gram)

Bacitracin zinc, USP 500 units

Neomycin Sulfate, USP 3.5 mg

Polymyxin B sulfate, USP 10,000 units

Pramoxine hydrochloride, USP 10 mg

OTC - PURPOSE

First aid antibiotic/Pain reliever

USES

First aid to help prevent infection and for temporary relief of pain or discomfort due to

- minor cuts
- scrapes
- burns

WARNINGS

For external use only

Allergy alert:

- do not use if allergic to any of the ingredients

OTC - DO NOT USE

- in the eyes
- over large areas of the body

OTC - ASK A DOCTOR BEFORE USE IF YOU HAVE

- deep or puncture wounds
- animal bites
- serious burns[/S][/S][/S]

OTC - WHEN USING THIS PRODUCT

- do not use longer than 1 week unless directed by a doctor

OTC - STOP USE AND ASK A DOCTOR IF

- condition persists or gets worse
- symptoms last for more than 7 days or clear up and come back within a few days
- a rash or other allergic reaction develops

OTC - KEEP OUT OF REACH OF CHILDREN

If swallowed, get medical help or contact a Poison Control Center right away.

2 DOSAGE & ADMINISTRATION

Adults and children 2 years and older:

- clean affected area
- apply a small amount of this product (an amount equal to the surface area of the tip of a finger) on area 1 to 3 times daily
- may be covered with a sterile bandage

Children under 2 years: ask a doctor

OTHER INFORMATION

- Store at 59º -86ºF (15º -30ºC).
- Before using any medication, read all label directions. Keep carton, it contains important information.

INACTIVE INGREDIENT

White petrolatum

OTC - QUESTIONS OR COMMENTS?

1-800-632-6900

PACKAGE LABEL.PRINCIPAL DISPLAY PANEL

Kroger®

QUALITY GUARANTEED

Compare to the active ingredients of NEOSPORIN® PLUS.

*See Back Panel.

maximum strength

TRIPLE ANTIBIOTIC OINTMENT

PLUS PAIN RELIEF

• Bacitracin Zinc • Neomycin Sulfate • Polymyxin B Sulfate • Pramoxine Hydrochloride

• First aid antibiotic plus topical pain reliever

NET WT 1 OZ (28 g)

08230611xx VC108014

CARTON LABEL